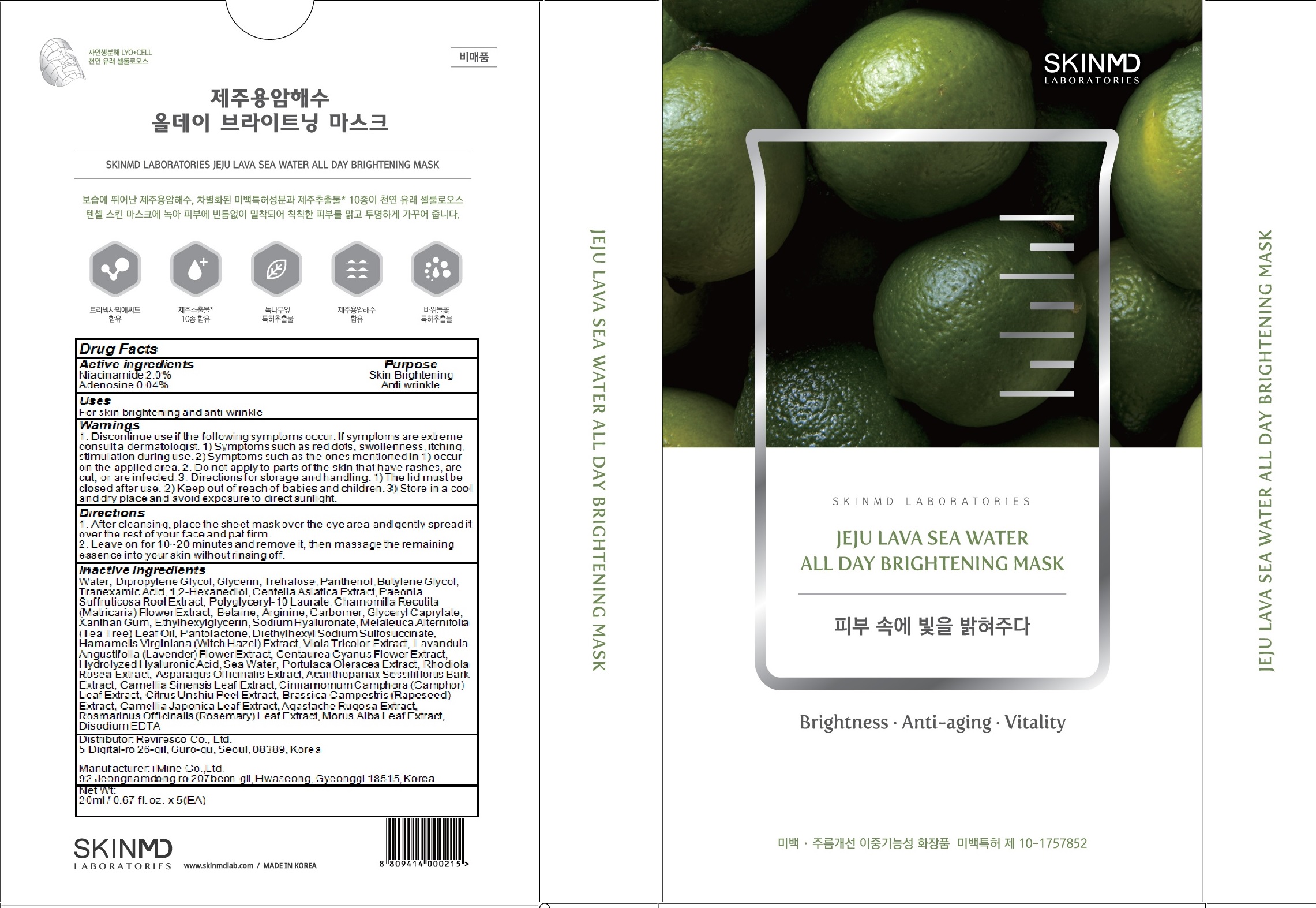 DRUG LABEL: JEJU LAVA SEA WATER ALL DAY BRIGHTENING MASK
NDC: 71974-050 | Form: PATCH
Manufacturer: Reviresco Co., Ltd.
Category: otc | Type: HUMAN OTC DRUG LABEL
Date: 20200106

ACTIVE INGREDIENTS: Niacinamide 0.4 g/20 mL; Adenosine 0.008 g/20 mL
INACTIVE INGREDIENTS: Water; Dipropylene Glycol

ACTIVE INGREDIENT

Active ingredients: Niacinamide 2.0%, Adenosine 0.04%

INACTIVE INGREDIENT

Inactive ingredients:

Water, Dipropylene Glycol, Glycerin, Trehalose, Panthenol, Butylene Glycol, Tranexamic Acid, 1,2-Hexanediol, Centella Asiatica Extract, Paeonia Suffruticosa Root Extract, Polyglyceryl-10 Laurate, Chamomilla Recutita (Matricaria) Flower Extract, Betaine, Arginine, Carbomer, Glyceryl Caprylate, Xanthan Gum, Ethylhexylglycerin, Sodium Hyaluronate, Melaleuca Alternifolia (Tea Tree) Leaf Oil, Pantolactone, Diethylhexyl Sodium Sulfosuccinate, Hamamelis Virginiana (Witch Hazel) Extract, Viola Tricolor Extract, Lavandula Angustifolia (Lavender) Flower Extract, Centaurea Cyanus Flower Extract, Hydrolyzed Hyaluronic Acid, Sea Water, Portulaca Oleracea Extract, Rhodiola Rosea Extract, Asparagus Officinalis Extract, Acanthopanax Sessiliflorus Bark Extract, Camellia Sinensis Leaf Extract, Cinnamomum Camphora (Camphor) Leaf Extract, Citrus Unshiu Peel Extract, Brassica Campestris (Rapeseed) Extract, Camellia Japonica Leaf Extract, Agastache Rugosa Extract, Rosmarinus Officinalis (Rosemary) Leaf Extract, Morus Alba Leaf Extract, Disodium EDTA

PURPOSE

Purpose: Skin Brightening, Anti wrinkle

WARNINGS

1. Discontinue use if the following symptoms occur. If symptoms are extreme consult a dermatologist. 1) Symptoms such as red dots, swollenness, itching, stimulation during use. 2) Symptoms such as the ones mentioned in 1) occur on the applied area. 2. Do not apply to parts of the skin that have rashes, are cut, or are infected. 3. Directions for storage and handling. 1) The lid must be closed after use. 2) Keep out of reach of babies and children. 3) Store in a cool and dry place and avoid exposure to direct sunlight.

KEEP OUT OF REACH OF CHILDREN

Keep out of reach of babies and children.

Uses

For skin brightening and anti-wrinkle

Directions

1. After cleansing, place the sheet mask over the eye area and gently spread it over the rest of your face and pat firm.
2. Leave on for 10~20 minutes and remove it, then massage the remaining essence into your skin without rinsing off.